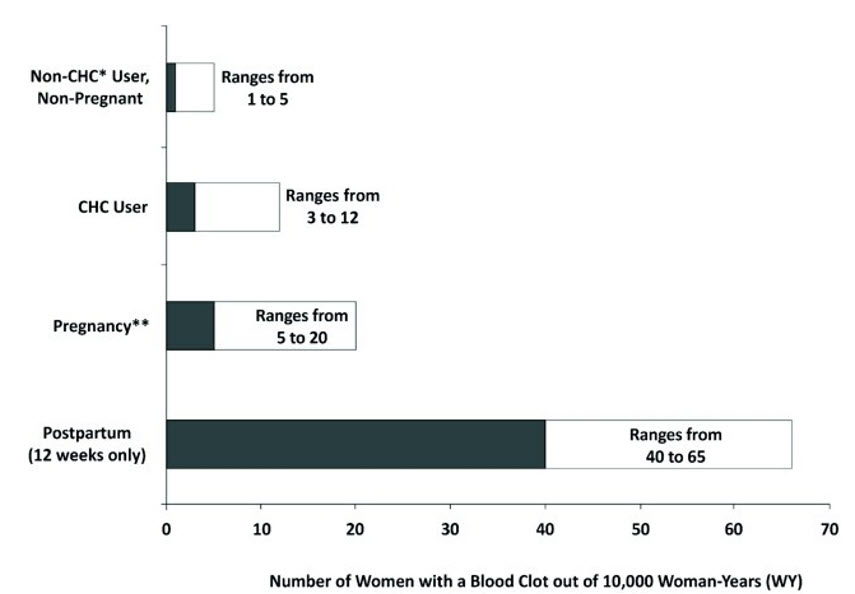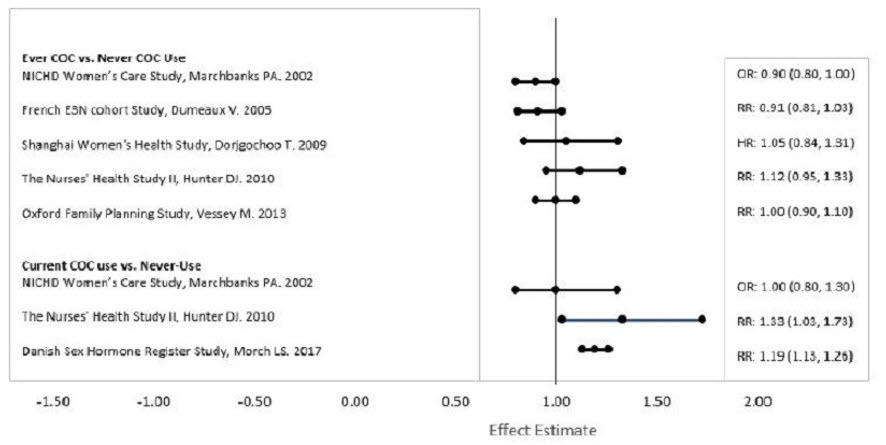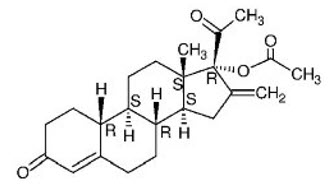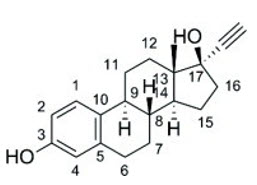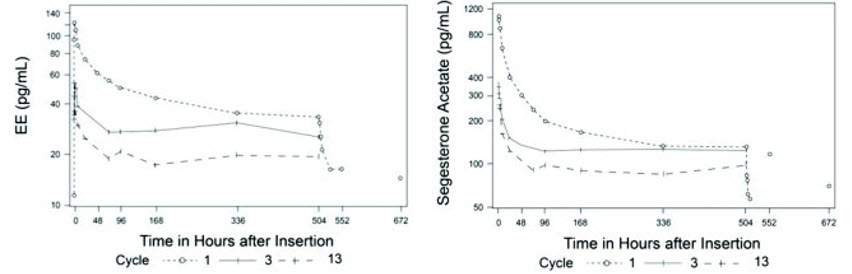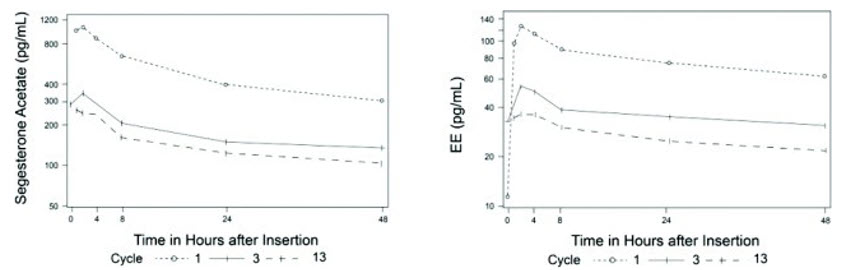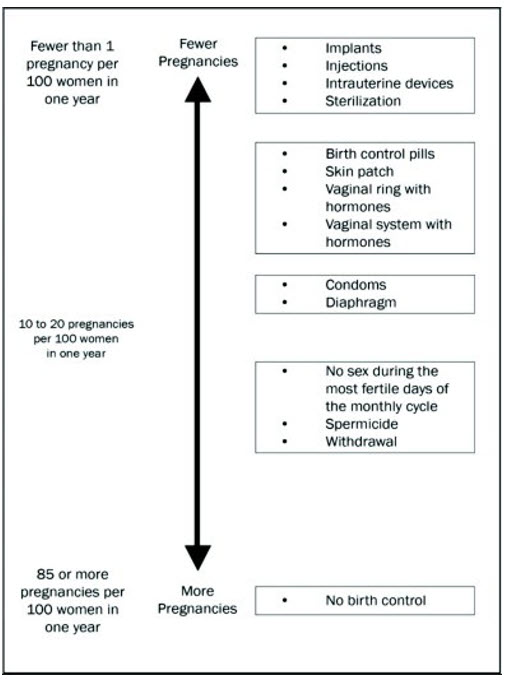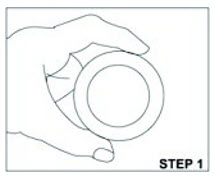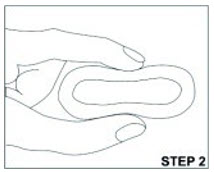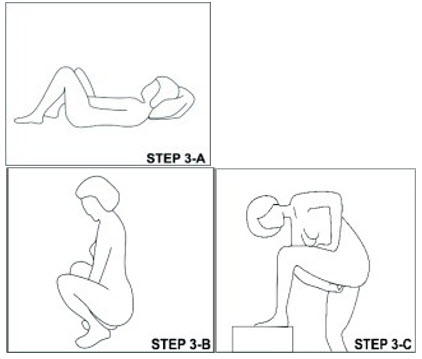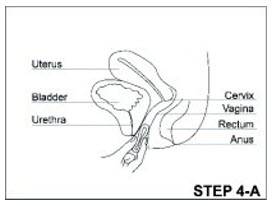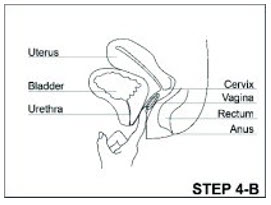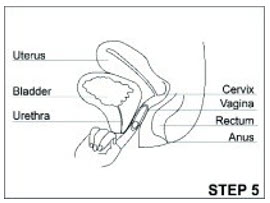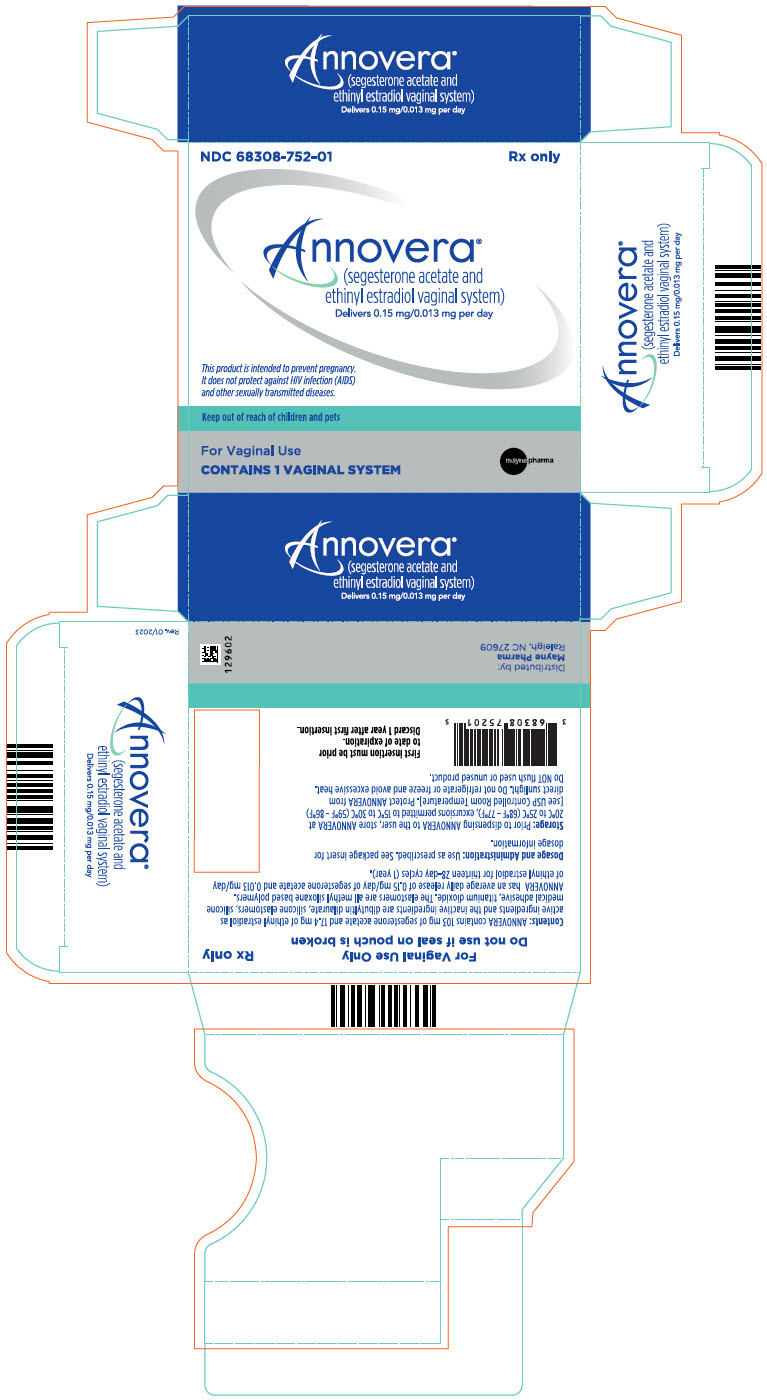 DRUG LABEL: Annovera
NDC: 68308-752 | Form: RING
Manufacturer: Mayne Pharma
Category: prescription | Type: HUMAN PRESCRIPTION DRUG LABEL
Date: 20250423

ACTIVE INGREDIENTS: segesterone acetate 103 mg/1 1; ethinyl estradiol 17.4 mg/1 1
INACTIVE INGREDIENTS: titanium dioxide; dibutyltin dilaurate

HIGHLIGHTS OF PRESCRIBING INFORMATION

These highlights do not include all the information needed to use ANNOVERA safely and effectively.
See Full Prescribing Information for ANNOVERA
ANNOVERA® (segesterone acetate and ethinyl estradiol vaginal system)
Initial U.S. Approval: 2018

WARNING: CIGARETTE SMOKING AND SERIOUS CARDIOVASCULAR EVENTS

See full prescribing information for complete boxed warning.

- Females over 35 years old who smoke should not use ANNOVERA. (4)
- Cigarette smoking increases the risk of serious cardiovascular events from combination hormonal contraceptive (CHC) use. (4)

RECENT MAJOR CHANGES

Warnings and Precautions (5.11) | 04/2022

1 INDICATIONS AND USAGE

ANNOVERA is a progestin/estrogen CHC indicated for use by females of reproductive potential to prevent pregnancy. (1)

Limitations of Usage

Not adequately evaluated in females with a body mass index of >29 kg/m^2. (1)

2 DOSAGE AND ADMINISTRATION

One ANNOVERA is inserted in the vagina. The vaginal system must remain in place continuously for 3 weeks (21 days) followed by a 1-week (7-day) vaginal system-free interval. One vaginal system provides contraception for thirteen 28-day cycles (1 year). (2)

3 DOSAGE FORMS AND STRENGTHS

ANNOVERA is a silicone elastomer vaginal system containing 103 mg segesterone acetate (SA) and 17.4 mg ethinyl estradiol (EE), which releases on average 0.15 mg/day of segesterone acetate and 0.013 mg/day of ethinyl estradiol. (3)

4 CONTRAINDICATIONS

- A high risk of arterial or venous thrombotic diseases (4)
- Breast cancer (4)
- Liver tumors, acute hepatitis, or severe (decompensated) cirrhosis (4)
- Undiagnosed abnormal uterine bleeding (4)
- Hypersensitivity to any of the components of ANNOVERA (4)
- Use of Hepatitis C drug combinations containing ombitasvir/paritaprevir/ritonavir, with or without dasabuvir (4)

5 WARNINGS AND PRECAUTIONS

- Thrombotic Disorders and Other Vascular Problems: Stop ANNOVERA if a thrombotic or thromboembolic event occurs. Stop ANNOVERA at least 4 weeks before and through 2 weeks after major surgery. Start ANNOVERA no earlier than 4 weeks after delivery, in females who are not breastfeeding. Consider cardiovascular risk factors before initiating in all females, particularly those over 35 years. (5.1, 5.5)
- Liver Disease: Discontinue if jaundice occurs. (5.2)
- Risk of Liver Enzyme Elevations with Concomitant Hepatitis C Treatment: Stop ANNOVERA prior to starting therapy with the combination drug regimen ombitasvir/paritaprevir/ritonavir. ANNOVERA can be restarted 2 weeks following completion of this regimen. (5.3)
- Hypertension: Do not prescribe ANNOVERA for females with uncontrolled hypertension or hypertension with vascular disease. If used in females with well-controlled hypertension, monitor blood pressure and stop use if blood pressure rises significantly. (5.4)
- Carbohydrate and lipid metabolic effects: Monitor glucose in pre-diabetic and diabetic females taking ANNOVERA. Consider an alternate contraceptive method for females with uncontrolled dyslipidemias. (5.7)
- Headache: Evaluate significant change in headaches and discontinue ANNOVERA if indicated. (5.8)
- Bleeding Irregularities and Amenorrhea: May cause irregular bleeding or amenorrhea. Evaluate for other causes if irregular bleeding or amenorrhea persists. (5.9)

6 ADVERSE REACTIONS

The most common adverse reactions (>5%) are headache/migraine, nausea/vomiting, vulvovaginal mycotic infection/candidiasis, abdominal pain lower/upper, dysmenorrhea, vaginal discharge, urinary tract infection, breast tenderness/pain/discomfort, bleeding irregularities including metrorrhagia, diarrhea, genital pruritus. (6)

To report SUSPECTED ADVERSE REACTIONS, contact Mayne Pharma at 1-844-825-8500 or FDA at 1-800-FDA-1088 or www.fda.gov/medwatch.

7 DRUG INTERACTIONS

Drugs or herbal products that induce certain enzymes, including CYP3A4, may decrease the effectiveness of ANNOVERA or increase breakthrough bleeding. Counsel patients to use a back-up or alternative method of contraception when enzyme inducers are used with ANNOVERA. (7.1)

8 USE IN SPECIFIC POPULATIONS

- Pregnancy: Discontinue if pregnancy occurs. (8.1)
- Lactation: Not recommended for nursing mothers; can decrease milk production. (8.2)

FULL PRESCRIBING INFORMATION

WARNING: CIGARETTE SMOKING AND SERIOUS CARDIOVASCULAR EVENTS

Cigarette smoking increases the risk of serious cardiovascular events from combination hormonal contraceptive (CHC) use. This risk increases with age, particularly in females over 35 years of age, and with the number of cigarettes smoked. For this reason, CHC should not be used by females who are over 35 years of age and smoke. [See Contraindications (4) and Warnings and Precautions (5.5)].

1 INDICATIONS AND USAGE

ANNOVERA is indicated for use by females of reproductive potential to prevent pregnancy.

Limitations of Use

ANNOVERA has not been adequately studied in females with a BMI >29 kg/m^2.

2 DOSAGE AND ADMINISTRATION

2.1 How to Use ANNOVERA

Instruct patients that ANNOVERA should be used as directed [see How to Start ANNOVERA (2.2)]. One ANNOVERA should be placed in the vagina. For maximum contraceptive effectiveness, ANNOVERA is to remain in the vagina continuously for 21 days (3 complete weeks). It is removed for a 1-week dose-free interval, and during this time a withdrawal bleed usually occurs. The removed vaginal system should be cleaned with mild soap and warm water, patted dry with a clean cloth towel or paper towel, and placed in its case during the 1-week dose- free interval. At the end of the dose-free interval, the vaginal system should be cleaned prior to being placed back in the vagina for another 21 continuous days (3 complete weeks). This pattern of ANNOVERA use made up of 3-weeks in and 1-week out is a cycle of use; one ANNOVERA vaginal system will provide contraception for 13 cycles.

With clean hands, the user can choose an insertion position that is comfortable, such as lying down, squatting, or standing. The sides of the vaginal system are pressed together for insertion into the vagina. When properly inserted, the vaginal system should be entirely in the vagina and behind the pelvic bone. The day and time of insertion should be noted so that the vaginal system can be removed 3 weeks later on the same day and at about the same time.

ANNOVERA can be removed by hooking an index finger into the vaginal system inside the vagina and gently pulling the vaginal system.

For patient instructions regarding cleaning the vaginal system, see FDA-approved Patient Information.

2.2 How to Start ANNOVERA

IMPORTANT: Consider the possibility of ovulation and conception prior to the first use of ANNOVERA.

No Hormonal Contraceptive Use in the Preceding Cycle and after Copper IUD Removal:

The woman should insert ANNOVERA between days 2 and 5 of her regular menstrual bleeding; no back-up contraception is needed. If menstrual cycles are irregular or if the start is more than 5 days from the last menstrual bleeding, the woman should use an additional barrier method during coitus, such as a male condom or spermicide, for the first 7 days of ANNOVERA use.

Switching from a CHC:

A woman who has been using her CHC method consistently and correctly, and who you are reasonably certain is not already pregnant, may switch from her previous CHC to ANNOVERA on any day of the CHC cycle (Day 1-28), without the need for back-up contraception, but no more than 7 hormone-free days should occur before starting ANNOVERA.

Switching from a Progestin-Only Method [Progestin-only pills (POP), Progestin Injection, Progestin Implant, Progestin Intrauterine System (IUS)]:

If a woman has no contraindications to the use of ethinyl estradiol (EE), she may elect to switch from a progestin-only method to ANNOVERA. If switching from progestin-only pills, she should begin ANNOVERA at the time she would have taken her next POP pill. If switching from an injection, she should begin ANNOVERA at the time of her next scheduled injection. If switching from an implant or an IUS, she should begin ANNOVERA at the time of implant or IUS removal. In all of these cases, the woman should use an additional barrier method during coitus, such as a male condom or spermicide, for the first 7 days of ANNOVERA use.

Use after Abortion or Miscarriage:

If a woman has no contraindications to the use of EE, ANNOVERA may be initiated for contraception within the first 5 days following a complete first trimester abortion or miscarriage without additional back-up contraception. If more than 5 days have elapsed from the first trimester abortion or miscarriage, then follow the instructions for "No Hormonal Contraceptive Use in the Preceding Cycle" and a barrier method should be used from the time of the first trimester abortion or miscarriage to the initiation of ANNOVERA.

ANNOVERA should not be started earlier than 4 weeks after a second trimester abortion or miscarriage due to the increased risk of thromboembolism [see Contraindications (4) and Warnings and Precautions (5.1)].

Following Childbirth:

ANNOVERA should not be started sooner than 4 weeks postpartum and only in females who choose not to breastfeed. Prior to 4 weeks postpartum there is an increased risk of thromboembolism [see Contraindications (4) and Warnings and Precautions (5.1)].

The initiation of ANNOVERA 4 weeks or more postpartum should be accompanied by an additional method of contraception during coitus, such as male condoms or spermicide, for the first 7 days if the woman has not yet had a period. Consider the possibility of ovulation and conception occurring prior to initiating ANNOVERA.

Females who are breastfeeding should not use ANNOVERA until after weaning.

2.3 Deviations from the Recommended Regimen

Contraceptive efficacy of ANNOVERA may be reduced if a woman deviates from the recommended use. ANNOVERA should remain in the vagina for a continuous period of 21 days (3 weeks); then ANNOVERA should be taken out of the vagina for 7 days. In a 28-day cycle, a deviation that involves ANNOVERA being out of the vagina for less than 7 days will not increase pregnancy risk. In a 28-day cycle, a deviation that involves ANNOVERA being out of the vagina for more than 7 days will increase pregnancy risk and back-up contraception is recommended in these instances. Deviations from the recommended regimen may result in a new vaginal system change day [See FDA- approved Patient Information].

Inadvertent Removal or Expulsion

ANNOVERA can be accidently expelled. Accidental expulsion could occur while removing a tampon, during coitus, or with straining during a bowel movement. If the vaginal system is accidentally expelled once during the 21 days of intravaginal use and is replaced within 2 hours, contraceptive efficacy should not be reduced and no back-up contraception is needed. If the vaginal system is accidently expelled, wash it with mild soap and warm water, rinse and pat dry with a clean cloth towel or paper towel, and replace it as soon as possible.

During the 21 days of continuous use, if ANNOVERA is out of the vagina for more than 2 continuous hours or more than 2 cumulative hours (multiple inadvertent removals or expulsions adding up to 2 hours), then back-up contraception, such as male condoms or spermicide, should be used until the vaginal system has been in the vagina for 7 consecutive days. The use of combined hormonal contraceptives (those containing an estrogen) for emergency contraception during use of ANNOVERA is not recommended.

Prolonged Vaginal System Free Interval

If the vaginal system free interval is prolonged, consider the possibility of pregnancy and have the woman use back-up contraception, such as male condoms or spermicide, during coitus until the vaginal system has been in the vagina for 7 consecutive days. The use of combined hormonal contraceptives (those containing an estrogen) for emergency contraception during use of ANNOVERA is not recommended.

Prolonged Use of ANNOVERA

If ANNOVERA is left in the vagina for more than 21 days, it should be removed for 7 days and then reinserted for 21 days to resume a 21/7 schedule.

3 DOSAGE FORMS AND STRENGTHS

Vaginal system: Each ANNOVERA releases an approximate average 0.15 mg/day of segesterone acetate (SA) and 0.013 mg/day of ethinyl estradiol (EE) when placed in the vagina over a period of 21 days of each cycle for up to 13 cycles (total of 273 days). Each cycle of use is 28 days with 21 days in and 7 days out.

ANNOVERA (segesterone acetate and ethinyl estradiol vaginal system) is a toroidal- shaped (ring), nonbiodegradable, flexible, opaque white, contraceptive vaginal system containing 103 mg of SA and 17.4 mg EE.

ANNOVERA is 56 mm in overall diameter and 8.4 mm in cross-sectional diameter. It contains 2 channels of approximately 3.0 mm diameter and 27 mm length into which steroid-containing cores are inserted. The cores are 3 mm in diameter with one releasing SA alone and the other releasing both SA and EE.

Each ANNOVERA is designed to be used for up to 13 cycles (1 year).

ANNOVERA is not made with natural rubber latex.

4 CONTRAINDICATIONS

ANNOVERA is contraindicated in females who are known to have or develop the following conditions:

- A high risk of arterial or venous thrombotic diseases. Examples include females who are known to:
  - Smoke, if over age 35 [see Boxed Warning and Warnings and Precautions (5.1)].
  - Have current or history of deep vein thrombosis or pulmonary embolism [see Warnings and Precautions (5.1)].
  - Have cerebrovascular disease [see Warnings and Precautions (5.1)].
  - Have coronary artery disease [see Warnings and Precautions (5.1)].
  - Have thrombogenic valvular or thrombogenic rhythm diseases of the heart (for example, subacute bacterial endocarditis with valvular disease, or atrial fibrillation) [see Warnings and Precautions (5.1)].
  - Have inherited or acquired hypercoagulopathies [see Warnings and Precautions (5.1)].
  - Have uncontrolled hypertension or hypertension with vascular disease [see Warnings and Precautions (5.4)].
  - Have diabetes mellitus and are over age 35, diabetes mellitus with hypertension or vascular disease, or other end-organ damage, or diabetes mellitus of >20 years duration [see Warnings and Precautions (5.5), (5.7)].
  - Have headaches with focal neurological symptoms, migraine headaches with aura, or are over age 35 with any migraine headaches [see Warnings and Precautions (5.8)].
- Current diagnosis of, or history of, breast cancer, which may be hormone-sensitive [see Warnings and Precautions (5.11)].
- Liver tumors, acute hepatitis, or severe (decompensated) cirrhosis [see Warnings and Precautions (5.2) and Use in Specific Populations (8.6)].
- Undiagnosed abnormal uterine bleeding [see Warnings and Precautions (5.9)].
- Hypersensitivity to any of the components of ANNOVERA. Hypersensitivity reactions reported include: throat constriction, facial edema, urticaria, hives, and wheezing [see Adverse Reactions (6.1)].
- Use of Hepatitis C drug combinations containing ombitasvir/paritaprevir/ritonavir, with or without dasabuvir, due to the potential for alanine transaminase (ALT) elevations [see Warnings and Precautions (5.3)].

5 WARNINGS AND PRECAUTIONS

5.1 Thromboembolic Disorders and Other Vascular Conditions

Females are at increased risk for a venous thrombotic event (VTE) when using ANNOVERA. Limited data are available in females with a BMI >29.0 kg/m^2 because this subpopulation was excluded from the clinical trials after VTEs were reported.

- Stop ANNOVERA if an arterial or deep venous thrombotic event occurs.
- Stop ANNOVERA if there is unexplained loss of vision, proptosis, diplopia, papilledema, or retinal vascular lesions and evaluate for retinal vein thrombosis immediately.
- Discontinue ANNOVERA during prolonged immobilization. If feasible, stop ANNOVERA at least 4 weeks before and through 2 weeks after major surgery or other surgeries known to have an elevated risk of VTE.
- Start ANNOVERA no earlier than 4 weeks after delivery in females who are not breastfeeding. The risk of postpartum VTE decreases after the third postpartum week, whereas the risk of ovulation increases after the third postpartum week.
- Before starting ANNOVERA, evaluate any past medical history or family history of thrombotic or thromboembolic disorders and consider whether the history suggests an inherited or acquired hypercoagulopathy. ANNOVERA is contraindicated in females with a high risk of arterial or venous thrombotic/thromboembolic diseases [see Contraindications (4)].

Arterial Events

CHCs increase the risk of cardiovascular events and cerebrovascular events, such as stroke and myocardial infarction. The risk is greater among older females (>35 years of age), smokers, and females with hypertension, dyslipidemia, diabetes, or obesity.

ANNOVERA is contraindicated in females over 35 years of age who smoke [see Contraindications (4)]. Cigarette smoking increases the risk of serious cardiovascular events from CHC use. This risk increases with age, particularly in females over 35 years of age, and with the number of cigarettes smoked.

Venous Events

The use of CHCs increases the risk of VTE, such as deep vein thrombosis and pulmonary embolism. Risk factors for VTEs include smoking, obesity, and family history of VTE, in addition to other factors that contraindicate use of CHCs [see Contraindications (4)]. While the increased risk of VTE associated with use of CHCs is well established, the rates of VTE are even greater during pregnancy, and especially during the postpartum period (see Figure 1). The rate of VTE in females using CHCs has been estimated to be 3–12 cases per 10,000 woman-years.

The risk of VTE is highest during the first year of CHC use and when restarting hormonal contraception following a break of 4 weeks or longer. The risk of VTE due to CHCs gradually disappears after use is discontinued.

Figure 1 shows the risk of developing a VTE for females who are not pregnant and do not use CHCs, for females who use CHCs, for pregnant females, and for females in the postpartum period. To put the risk of developing a VTE into perspective: If 10,000 females who are not pregnant and do not use CHCs are followed for 1 year, between 1 and 5 of these women will develop a VTE.

Figure 1: Likelihood of Developing a VTE

* CHC = combination hormonal contraception
** Pregnancy data based on actual duration of pregnancy in the reference studies. Based on a model assumption that pregnancy duration is 9 months, the rate is 7 to 27 per 10,000 WY.

5.2 Liver Disease

Impaired Liver Function

ANNOVERA is contraindicated in females with acute hepatitis or severe (decompensated) cirrhosis of the liver [see Contraindications (4)]. Discontinue ANNOVERA if jaundice develops. Acute liver test abnormalities may necessitate the discontinuation of ANNOVERA use until the liver tests return to normal and ANNOVERA causation has been excluded.

Liver Tumors

ANNOVERA is contraindicated in females with benign or malignant liver tumors [see Contraindications (4)]. Hepatic adenomas are associated with CHC use. An estimate of the attributable risk is 3.3 cases/100,000 CHC users. Rupture of hepatic adenomas may cause death through intra-abdominal hemorrhage.

Studies have shown an increased risk of developing hepatocellular carcinoma in long- term (>8 years) CHC users. The attributable risk of liver cancers in CHC users is less than one case per million users.

5.3 Risk of Liver Enzyme Elevations with Concomitant Hepatitis C Treatment

During clinical trials with the Hepatitis C combination drug regimen that contains ombitasvir/paritaprevir/ritonavir, with and without dasabuvir, ALT elevations greater than 5 times the upper limit of normal (ULN), including some cases greater than 20 times the ULN, were significantly more frequent in females using ethinyl estradiol-containing medications, such as ANNOVERA. Discontinue ANNOVERA prior to starting therapy with the combination drug regimen ombitasvir/paritaprevir/ritonavir, with or without dasabuvir [see Contraindications (4)]. ANNOVERA can be restarted approximately 2 weeks following completion of treatment with the Hepatitis C combination drug regimen.

5.4 Hypertension

ANNOVERA is contraindicated in females with uncontrolled hypertension or hypertension with vascular disease [see Contraindications (4)]. For all females, including those with well- controlled hypertension, monitor blood pressure at routine visits and stop ANNOVERA if blood pressure rises significantly.

An increase in blood pressure has been reported in females using CHCs, and this increase is more likely in older females and with extended duration of use. The effect of CHCs on blood pressure may vary according to the progestin in the CHC.

5.5 Age-Related Considerations

The risk for cardiovascular disease and prevalence of risk factors for cardiovascular disease increase with age. Certain conditions, such as smoking and migraine headache without aura, that do not contraindicate CHC use in younger females, are contraindications to use in women over 35 years of age [see Contraindications (4) and Warnings and Precautions (5.1)]. Consider the presence of underlying risk factors that may increase the risk of cardiovascular disease or VTE, particularly before initiating ANNOVERA for women over 35 years, such as:

- Hypertension
- Diabetes
- Dyslipidemia
- Obesity

5.6 Gallbladder Disease

Studies suggest a small increased relative risk of developing gallbladder disease among CHC users. Use of CHCs may also worsen existing gallbladder disease.

A past history of CHC-related cholestasis predicts an increased risk with subsequent CHC use. Females with a history of pregnancy-related cholestasis may be at an increased risk for CHC- related cholestasis.

5.7 Adverse Carbohydrate and Lipid Metabolic Effects

Hyperglycemia

ANNOVERA is contraindicated in diabetic females over age 35, or females who have diabetes with hypertension, nephropathy, retinopathy, neuropathy, other vascular disease, or females with diabetes of >20 years duration [see Contraindications (4)]. ANNOVERA may decrease glucose tolerance. Carefully monitor prediabetic and diabetic females who are taking ANNOVERA.

Dyslipidemia

Consider alternative contraception for females with uncontrolled dyslipidemia. ANNOVERA may cause adverse lipid changes.

Females with hypertriglyceridemia, or a family history thereof, may be at an increased risk of pancreatitis when using ANNOVERA.

5.8 Headache

ANNOVERA is contraindicated in females who have headaches with focal neurological symptoms or have migraine headaches with aura, and in females over age 35 years who have migraine headaches with or without aura [see Contraindications (4)].

If a woman taking ANNOVERA develops new headaches that are recurrent, persistent, or severe, evaluate the cause and discontinue ANNOVERA if indicated.

Consider discontinuation of ANNOVERA in the case of increased frequency or severity of migraine during CHC use (which may be prodromal of a cerebrovascular event) [see Contraindications (4)].

5.9 Bleeding Irregularities and Amenorrhea

Bleeding and/or spotting that occurs at any time while the vaginal system is inserted is considered "unscheduled" bleeding/spotting. Bleeding/spotting that occurs during the dose-free week when the vaginal system is out is considered "scheduled" bleeding.

Unscheduled and Scheduled Bleeding and Spotting

Females using ANNOVERA may experience unscheduled (breakthrough) bleeding and spotting, especially during the first month of use. If unscheduled bleeding persists or occurs after previously regular cycles on ANNOVERA, check for causes such as pregnancy or malignancy. If pathology and pregnancy are excluded, bleeding irregularities may resolve over time or with a change to a different CHC.

Based on subject diaries from the two clinical efficacy trials of ANNOVERA [see Clinical Trial Experience (6.1)], 5–10% of females experienced unscheduled bleeding per 28-day cycle. The average number of days with unscheduled bleeding and/or spotting, in Treatment Cycles 1 to 13 for those females who experienced unscheduled bleeding and/or spotting, was 1 day or less per cycle. A total of 41 subjects (1.7%) discontinued use due to menstrual disorders including metrorrhagia, menorrhagia, and abnormal withdrawal bleeding.

Amenorrhea and Oligomenorrhea

Females who are not pregnant and use ANNOVERA may experience amenorrhea. Based on subject diary data from two clinical trials for up to 13 cycles, amenorrhea occurred in 3–5% of females per cycle using ANNOVERA and in 0.9% of females in all 13 cycles.

If scheduled bleeding does not occur, consider the possibility of pregnancy. If the patient has not adhered to the prescribed dosing schedule (removed vaginal system for >2 hours during the first 21 days or does not replace after 7 days of vaginal system- free period), consider the possibility of pregnancy at the time of the first missed period and perform a pregnancy test. If the patient has adhered to the prescribed dosing schedule and misses 2 consecutive periods, perform a pregnancy test to rule out pregnancy.

Some females may experience amenorrhea or oligomenorrhea after stopping ANNOVERA, especially when such a condition was pre-existent.

5.10 Depression

Carefully observe females with a history of depression and discontinue ANNOVERA if depression recurs to a serious degree. Data on the association of CHCs with onset of depression or exacerbation of existing depression are limited.

5.11 Malignant Neoplasms

Breast Cancer

Annovera is contraindicated in females who currently have or have had breast cancer because breast cancer may be hormonally sensitive [see Contraindications (4)].

Epidemiology studies have not found a consistent association between use of combined oral contraceptives (COCs) and breast cancer risk. Studies do not show an association between ever (current or past) use of COCs and risk of breast cancer. However, some studies report a small increase in the risk of breast cancer among current or recent users (<6 months since last use) and current users with longer duration of COC use [see Postmarketing Experience (6.2)].

Cervical Cancer

Some studies suggest that CHCs are associated with an increase in the risk of cervical cancer or intraepithelial neoplasia. However, there is controversy about the extent to which these findings are due to differences in sexual behavior and other factors.

5.12 Effect on Binding Globulins

The estrogen component of ANNOVERA may raise the serum concentrations of thyroxine- binding globulin, sex hormone-binding globulin, and cortisol-binding globulin. The dose of replacement thyroid hormone or cortisol therapy may need to be increased.

5.13 Hereditary Angioedema

In females with hereditary angioedema, exogenous estrogens may induce or exacerbate symptoms of angioedema.

5.14 Chloasma

Chloasma may occur with ANNOVERA use, especially in females with a history of chloasma gravidarum. Advise females who tend to develop chloasma to avoid exposure to the sun or ultraviolet radiation while using ANNOVERA.

5.15 Toxic Shock Syndrome (TSS)

Cases of TSS have been reported by vaginal ring users. TSS has been associated with tampons and certain barrier contraceptives, and in some TSS cases ring users were also using tampons. Causal relationship between the use of a vaginal ring and TSS has not been established. No cases of TSS occurred in clinical trials with ANNOVERA. If a patient exhibits signs or symptoms of TSS, consider the possibility of this diagnosis, remove ANNOVERA, and initiate appropriate medical evaluation and treatment.

5.16 Vaginal Use

Some females are aware of the vaginal system on occasion during the 21 days of use or during coitus, and partners may feel the vaginal system during coitus.

There is no information on the concomitant use of ANNOVERA with diaphragms, cervical caps, and female condoms.

ANNOVERA may not be suitable for females with conditions that make the vagina more susceptible to vaginal irritation or ulceration. Vaginal and cervical erosion and/or ulceration has been reported in females using other contraceptive vaginal devices. In some cases, the ring adhered to vaginal tissue, which necessitated removal by a healthcare provider.

6 ADVERSE REACTIONS

The following adverse reactions are described elsewhere in other sections of the labeling:

- Serious cardiovascular events and stroke [see Boxed Warning and Warnings and Precautions (5.1)]
- Vascular events [see Warnings and Precautions (5.1)]
- Liver disease [see Warnings and Precautions (5.2)]

6.1 Clinical Trial Experience

Because clinical trials are conducted under widely varying conditions, adverse reaction rates observed in the clinical trials of a drug cannot be directly compared to the rates in the clinical trials of another drug and may not reflect the rates observed in practice.

The clinical trials that evaluated the safety of ANNOVERA were obtained from three 13- cycle trials. One trial was conducted entirely in the U.S. (15 sites), and the other two were global studies that included 5 U.S. sites and 7 international sites (Australia, Brazil, Chile, Dominican Republic, Finland, Hungary, Sweden). All three trials were open label and enrolled healthy females, desiring contraception, 18 to 40 years of age. At about 50% enrollment, females with BMI >29 kg/m^2 were excluded due to the occurrence of two VTEs in this subgroup. In total, 2,308 females contributed 21,590 cycles of exposure for safety evaluation and 999 completed 13 cycles; there were 209 subjects with BMI >29 kg/m^2 who contributed 1,254 cycles of exposure with 36 subjects completing 13 cycles. The demographic profile for subjects was: mean age 26.7 years, mean BMI 24.1 (16.0- 41.5) kg/m^2; 67% were from the U.S. The racial distribution was 71% Caucasian, 14% African American, 4% Asian, and 11% Other; 30% of the population was Hispanic.

Most Common Adverse Reactions

Table 1 summarizes the most common adverse reactions reported by females using ANNOVERA. This table shows adverse reactions reported in at least 5% of subjects. In addition, 25% of subjects reported at least 1 complete expulsion during their use of ANNOVERA.

Table 1: Adverse Drug Reactions Reported by ≥ 5% of ANNOVERA-treated Subjects
Adverse Reactions | % (N=2,308)
Headache, including migraine | 38.6
Nausea/vomiting | 25.0
Vulvovaginal mycotic infection/vaginal candidiasis | 14.5
Abdominal pain/lower/upper | 13.3
Dysmenorrhea | 12.5
Vaginal discharge | 11.8
UTI/cystitis/pyelonephritis/genitourinary tract infection | 10.0
Breast pain/tenderness/discomfort | 9.5
Metrorrhagia/menstrual disorder | 7.5
Diarrhea | 7.2
Genital pruritus | 5.5

Adverse Reactions Leading to Discontinuation

Among subjects using ANNOVERA for contraception, 12% discontinued from the clinical trials due to an adverse reaction. Table 2 summarizes the most common adverse reactions leading to discontinuation. In addition, 1.4% of subjects discontinued ANNOVERA use due to vaginal system expulsions.

Table 2: Adverse Reactions Leading to Discontinuation by ≥ 1% of ANNOVERA treated Subjects
Adverse Reactions | % (N=2,308)
Metrorrhagia/menorrhagia | 1.7
Headache, including migraine | 1.3
Vaginal discharge/vulvovaginal mycotic infections | 1.3
Nausea/vomiting | 1.2

Serious Adverse Reactions

Serious adverse reactions occurring in ≥2 subjects were: VTEs (deep venous thrombosis, cerebral vein thrombosis, pulmonary embolism); psychiatric events; drug hypersensitivity reactions; and spontaneous abortions.

6.2 Postmarketing Experience

Five studies that compared breast cancer risk between ever-users (current or past use) of COCs and never-users of COCs reported no association between ever use of COCs and breast cancer risk, with effect estimates ranging from 0.90 - 1.12 (Figure 2).

Three studies compared breast cancer risk between current or recent COC users (<6 months since last use) and never users of COCs (Figure 2). One of these studies reported no association between breast cancer risk and COC use. The other two studies found an increased relative risk of 1.19 - 1.33 with current or recent use. Both of these studies found an increased risk of breast cancer with current use of longer duration, with relative risks ranging from 1.03 with less than one year of COC use to approximately 1.4 with more than 8-10 years of COC use.

Figure 2: Relevant Studies of Risk of Breast Cancer with Combined Oral Contraceptives

RR = relative risk; OR = odds ratio; HR = hazard ratio. "ever COC" are females with current or past COC use; "never COC use" are females who never used COCs.

7 DRUG INTERACTIONS

The sections below provide information on substances for which data on drug interactions with CHCs are available. There is little information available about the clinical effect of most drug interactions that may affect ANNOVERA. However, based on the known pharmacokinetic effects of these drugs, clinical strategies to minimize any potential adverse effect on contraceptive effectiveness or safety are suggested.

Consult the approved product labeling of all concurrently used drugs to obtain further information about interactions with ANNOVERA or the potential for metabolic enzyme or transporter system alterations.

7.1 Effects of Other Drugs on Combined Hormonal Contraceptives

Substances Decreasing the Systemic Exposure of CHCs and Potentially Diminishing the Efficacy of ANNOVERA: Table 3 includes substances that demonstrated an important drug interaction with CHCs.

Table 3: Significant Drug Interactions Involving Substances That Decrease Systemic Exposure of CHCs
Metabolic Enzyme Inducers
Clinical effect | - Concomitant use of CHCs with metabolic enzyme inducers may decrease the systemic concentrations of the estrogen and/or progestin component of CHCs [see Clinical Pharmacology (12.3)]. - Decreased exposure of the estrogen and/or progestin component of CHCs may potentially diminish the effectiveness of CHCs and may lead to contraceptive failure or an increase in breakthrough bleeding.
Prevention or management | - Counsel females to use an alternative method of contraception or a back-up method when enzyme inducers are used with CHCs. - Continue back-up contraception for 28 days after discontinuing the enzyme inducer to maintain contraceptive reliability.
Examples | Aprepitant, barbiturates, bosentan, carbamazepine, efavirenz, felbamate, griseofulvin, oxcarbazepine, phenytoin, rifampin, rifabutin, rufinamide, topiramate, products containing St. John's wort [Induction potency of St. John's wort may vary widely based on preparation.] , and certain protease inhibitors (see separate section on protease inhibitors below).

Substances Increasing the Systemic Exposure of CHCs and Potentially Increasing Exposure to Estrogen and/or Progestin in ANNOVERA: Co- administration of atorvastatin or rosuvastatin and certain CHCs containing EE increase systemic exposure of EE by approximately 20–25%. Ascorbic acid and acetaminophen may increase plasma EE concentrations, possibly by inhibition of conjugation. CYP3A4 inhibitors such as itraconazole, voriconazole, fluconazole, grapefruit juice, or ketoconazole may increase systemic exposure of the estrogen and/or progestin component of ANNOVERA.

Human Immunodeficiency Virus (HIV)/ Hepatitis C Virus (HCV) Protease Inhibitors and Non-nucleoside Reverse Transcriptase Inhibitors: Significant decreases in systemic exposure of estrogen and/or progestin have been noted when CHCs are co-administered with some HIV protease inhibitors (eg, nelfinavir, ritonavir, darunavir/ritonavir, (fos)amprenavir/ritonavir, lopinavir/ritonavir, and tipranavir/ritonavir), some HCV protease inhibitors (eg, boceprevir and telaprevir), and some non-nucleoside reverse transcriptase inhibitors (eg, nevirapine).

In contrast, significant increases in systemic exposure of estrogen and/or progestin have been noted when CHCs are co-administered with certain other HIV protease inhibitors (eg, indinavir and atazanavir/ritonavir) and with other non-nucleoside reverse transcriptase inhibitors (eg, etravirine).

7.2 Effects of Combined Hormonal Contraceptives on Other Drugs

Table 4 provides significant drug interaction information for drugs co-administered with CHCs.

Table 4: Significant Drug Interaction Information for Drugs Co-Administered with CHCs
Lamotrigine
Clinical effect | Concomitant use of CHCs with lamotrigine may significantly decrease systemic exposure of lamotrigine due to induction of lamotrigine glucuronidation.
Prevention or management | Dose adjustment for lamotrigine may be necessary. Consult the approved product labeling for lamotrigine.
Thyroid Hormone Replacement Therapy or Corticosteroid Replacement Therapy
Clinical effect | Concomitant use of CHCs with thyroid hormone replacement therapy or corticosteroid replacement therapy may increase systemic exposure of thyroid-binding and cortisol-binding globulin [see Warnings and Precautions (5.12)].
Prevention or management | The dose of replacement thyroid hormone or cortisol therapy may need to be increased. Consult the approved product labeling for the therapy in use [see Warnings and Precautions (5.12)].
Other Drugs
Clinical effect | Concomitant use of CHCs may decrease systemic exposure of acetaminophen, morphine, salicylic acid, and temazepam. Concomitant use with ethinyl estradiol-containing CHCs may increase systemic exposure of other drugs (eg, cyclosporine, prednisolone, theophylline, tizanidine, and voriconazole).
Prevention or management | The dosage of drugs that can be affected by this interaction may need to be increased or decreased. Consult the approved product labeling for the concomitantly used drug.

7.3 Use of Vaginal Products with ANNOVERA

In a drug-drug interaction study with ANNOVERA and the concurrent use of three different formulations of vaginal miconazole, the use of water-based vaginal miconazole cream resulted in no change in exposure to EE or SA from the vaginal system. However, the use of either the 1- day or the 3-day oil-based miconazole suppository was associated with an overall increase in exposure up to 67% for EE and 32% for SA. Considering the potential long-term effect on vaginal system performance, concurrent use of oil-based vaginal suppositories should not occur with ANNOVERA use. If there is a need to treat a vaginal condition, water-based vaginal cream or oral therapy may be used concurrently with the vaginal system [see Clinical Pharmacology (12.3)].

Lubricants: Water-based vaginal lubricants have no effect on ANNOVERA; however, oil- based (including silicone-based) vaginal lubricants will alter the vaginal system and/or exposure to EE and SA and should not be used.

ANNOVERA use is compatible with male condoms made with natural rubber latex, polyisoprene, and polyurethane.

The effect of tampon use on the systemic exposure of SA and EE from ANNOVERA has not been studied.

7.4 Concomitant Use with HCV Combination Therapy – Liver Enzyme Elevation

Do not co-administer ANNOVERA with HCV drug combinations containing ombitasvir/paritaprevir/ritonavir, with or without dasabuvir, due to potential for ALT elevations [see Contraindications (4) and Warnings and Precautions (5.3)].

7.5 Interference with Laboratory Tests

The use of contraceptive steroids may influence the results of certain laboratory tests, such as coagulation factors, lipids, glucose tolerance, and binding proteins.

8 USE IN SPECIFIC POPULATIONS

8.1 Pregnancy

Risk Summary

Epidemiologic studies and meta-analyses have not found an increased risk of genital or nongenital birth defects (including cardiac anomalies and limb-reduction defects) following exposure to CHCs before conception or during early pregnancy.

In the U.S. general population, the estimated background risk of major birth defects and miscarriage in clinically recognized pregnancies is 2–4% and 15–20%, respectively.

Discontinue ANNOVERA if pregnancy occurs, because there is no reason to use CHCs during pregnancy.

Data

Human Data

No studies have been conducted of the use of ANNOVERA in pregnant females.

8.2 Lactation

Risk Summary

Contraceptive hormones and/or metabolites are present in human milk. CHCs can reduce milk production in breastfeeding females. This reduction can occur at any time but is less likely to occur once breastfeeding is well established. Advise the nursing female to use another method of contraception until she discontinues breastfeeding [see Dosage and Administration (2.2)].

Data

Human Data

No studies have been conducted of the use of ANNOVERA in breastfeeding females. Two studies have been conducted in breastfeeding females of segesterone acetate implants delivering lower levels of segesterone acetate than ANNOVERA. Maternal serum levels of up to 141 pg/mL were associated with infant exposure of up to 7 pg/mL. No safety signals in feeding, growth, and development were observed in the infants between the segesterone acetate implant group and the control group.

8.4 Pediatric Use

Safety and efficacy of ANNOVERA have been established in women of reproductive age. Efficacy is expected to be the same for postpubertal adolescents under the age of 18 as for users 18 years and older. Use of ANNOVERA before menarche is not indicated.

8.5 Geriatric Use

ANNOVERA has not been studied in females who have reached menopause and is not indicated in this population.

8.6 Hepatic Impairment

No studies have been conducted to evaluate the effect of hepatic impairment on the disposition of ANNOVERA. However, steroid hormones may be poorly metabolized in patients with hepatic impairment. Acute or chronic disturbances of liver function may necessitate the discontinuation of CHC use until markers of liver function return to normal and CHC causation has been excluded [see Contraindications (4) and Warnings and Precautions (5.2)].

8.7 Renal Impairment

No studies were conducted in subjects with renal impairment; ANNOVERA is not recommended in patients with renal impairment.

8.8 Body Mass Index (BMI)/Body Weight

The safety and efficacy of ANNOVERA in females with a BMI >29 kg/m^2 have not been adequately evaluated because this subpopulation was excluded from the clinical trials after 2 VTEs occurred in females with a BMI > 29 kg/m^2 [see Adverse Reactions (6.1) and Clinical Studies (14)]. Higher body weight is associated with lower systemic exposure of SA and EE [see Clinical Pharmacology (12.3)].

10 OVERDOSAGE

There have been no reports of serious ill effects from overdose of CHCs. Overdosage may cause withdrawal bleeding in females and nausea. In case of suspected overdose, all ANNOVERA vaginal systems should be removed and symptomatic treatment given.

11 DESCRIPTION

ANNOVERA (segesterone acetate and ethinyl estradiol vaginal system) is a toroidal- shaped (ring), nonbiodegradable, flexible, opaque white vaginal system containing two active components, a progestin, segesterone acetate, and an estrogen, ethinyl estradiol. When placed in the vagina, each ANNOVERA releases an approximate average 0.15 mg/day of segesterone acetate and 0.013 mg/day of ethinyl estradiol over the 21 days in-use period of each cycle for up to 13 cycles (total of 273 days). Each cycle is 28 days, with 21 days in and 7 days out.

The inactive ingredients are dibutyltin dilaurate, silicone elastomers, silicone medical adhesive, and titanium dioxide. The elastomers are all methyl siloxane-based polymers.

The vaginal system body has an overall diameter of 56 mm and a cross-sectional diameter of 8.4 mm. It contains two channels of approximately 3.0 mm diameter and 27 mm length into which steroid-containing cores are inserted. Each ANNOVERA contains 103 mg of SA distributed throughout both cores and 17.4 mg of EE distributed throughout only one core. The core containing 40% SA and 12% EE of its mass is 3 mm in diameter and 18 mm in length. The core containing 50% SA of its mass is 3 mm in diameter and 11 mm in length. Contact between the cores and the vaginal system body is fixed by coating the channels with silicone medical adhesive before introducing the cores. After insertion of the cores, the channels are sealed with the silicone medical adhesive.

The structural formulas, and properties for the active components are shown below:

STRUCTURAL FORMULAS:

Segesterone Acetate (SA)

Ethinyl Estradiol (EE)

PROPERTIES:
Established Name: Segesterone Acetate
Chemical Name: 16-methylene-17α-acetoxy-19-nor-pregn-4-ene-3,20-dione
Molecular Formula: C23H30O4
Molecular Weight: 370.5
Physical Form: White, or yellowish white powder
Solubility: Slightly soluble in n-hexane, soluble in ethyl acetate and methanol, freely soluble in acetone (USP classification)
Melting Point: 173°C–177°C

Established Name: Ethinyl Estradiol
Chemical Name: 19-Nor-17α -pregna-1,3,5(10)-trien-20-yne-3,17-diol
Molecular Formula: C20H24O2
Molecular Weight: 296.4
Physical Form: White to slightly yellowish-white crystalline powder
Solubility: Practically insoluble in water, freely soluble in alcohol, it dissolves in alkaline solution
Melting Point: 181°C–185°C

The steroids diffuse out of the vaginal system with release rates that vary over time. Based on in vitro data, the daily release rates of SA and EE are higher during each initial 24–48 hours of use achieving a somewhat lower steady-state with continued use over the subsequent days in each cycle. The vaginal system is designed to be used for 13 cycles (1 year) on a 21/7 days in/out schedule. The total in-use time with the 21/7 days in/out schedule over 13 cycles is 273 days. Based on the residual amount of drug in vaginal systems used in clinical trials over 13 cycles, a total of 41.3 mg of SA and 3.4 mg of EE are released over this period. This translates to an approximate average daily dose of 0.15 mg of segesterone acetate and 0.013 mg of ethinyl estradiol with higher release rate expected at the beginning of dosing and a lower release rate toward the end.

12 CLINICAL PHARMACOLOGY

12.1 Mechanism of Action

CHCs lower the risk of becoming pregnant primarily by suppressing ovulation.

12.2 Pharmacodynamics

Cardiac Electrophysiology

The effect of SA on the QTc interval was evaluated in a Phase 1 randomized, placebo and positive controlled, double-blind, single-dose, three-period, crossover thorough QTc study in 44 healthy adult female subjects. At the single intravenous bolus dose which produces 4.5-fold the therapeutic serum concentrations of SA achieved with ANNOVERA, SA did not prolong the QTc interval to any clinically relevant extent.

12.3 Pharmacokinetics

Absorption

The pharmacokinetics (PK) of ANNOVERA were determined in 39 women who used ANNOVERA for up to 13 cycles. Following vaginal administration, SA and EE were absorbed into systemic circulation with median tmax of about 2 hours in Cycle 1, Cycle 3, and Cycle 13. Concentrations of both components declined after tmax and became more constant after 96 hours post-dose. Over subsequent cycles of use, the peak serum concentrations of SA and EE declined. Serum concentration-time profiles of SA and EE for Cycles 1, 3, and 13 of ANNOVERA use are provided in Figure 2 and Figure 3 with PK parameters summarized in Table 5 and Table 6.

Figure 3: Mean SA and EE Serum Concentrations Delivered by ANNOVERA Over 21 Days of Dosing for Cycles 1, 3, and 13

Figure 4: Mean SA and EE Serum Concentrations Delivered by ANNOVERA Over the First 48 Hours of Dosing for Cycles 1, 3, and 13

Table 5: Mean (SD) PK Parameters for SA following ANNOVERA Administration
Cycle | AUC0-21 day (ng*hr/mL) | AUC0-1 day (ng*hr/mL) | Cmax (pg/mL) | Cavg (pg/mL)
1 | 96.2 (16.9) | 15 (3.2) | 1,147 (315) | 191 (34)
3 | 65.9 (14.8) | 5 (1.6) | 363 (133) | 131 (29)
13 | 47.2 (10.1) | 3.9 (1.4) | 294 (116) | 94 (20)

Table 6: Mean (SD) PK Parameters for EE following ANNOVERA Administration
Cycle | AUC0-21 day (ng*hr/mL) | AUC0-1 day (ng*hr/mL) | Cmax (pg/mL) | Cavg (pg/mL)
1 | 22.2 (9.8) | 2.1 (0.7) | 129 (39) | 44 (19)
3 | 14.7 (4.7) | 0.9 (0.4) | 60 (32) | 29 (9)
13 | 9.6 (4.1) | 0.7 (0.3) | 39 (16) | 19 (8)

Distribution

The volume of distribution of SA is 19.6 L/kg. SA is approximately 95% bound to human serum proteins and has negligible binding affinity for sex hormone-binding globulin (SHBG). EE is highly protein bound but not specifically bound to serum albumin (98.5%) and induces an increase in the serum concentrations of SHBG.

Metabolism

In vitro data show that both SA and EE are metabolized by the cytochrome P450 (CYP) 3A4 isoenzyme. In human serum, two oxidative metabolites (5α-dihydro- and 17α- hydroxy-5α-dihydro metabolites) constitute 50% of exposure relative to SA. Both metabolites are not considered as active metabolites with EC50 to progesterone receptor 10-fold higher than that of SA. EE is primarily metabolized by aromatic hydroxylation, but a wide variety of hydroxylated and methylated metabolites are formed. These are present as free metabolites and as sulfate and glucuronide conjugates. The hydroxylated EE metabolites have weak estrogenic activity.

Excretion

The mean (SD) half-life of SA is 4.5 (3.4) hours. EE is known to be excreted in the urine and feces as glucuronide and sulfate conjugates, and it undergoes enterohepatic recirculation. The mean (SD) half-life of EE is 15.1 (7.5) hours.

Specific Populations

Body Mass Index (BMI)

Higher body weight associates with lower systemic exposure of SA and EE. In a PK study conducted in 18 females with BMI <25 (16.89–24.34) kg/m^2 and 21 females with BMI >25 (25.15–37.46) kg/m^2, up to 16% and 33% decreases in the systemic exposure (AUC0- 21day) of SA and EE, respectively, were observed between the two BMI groups.

Interaction with Vaginal Medications

A clinical drug-drug interaction (DDI) study was conducted to evaluate the effect of vaginal antimycotic medication (miconazole nitrate) on the PK of SA and EE in 29 females using ANNOVERA. The results showed that a single-dose vaginal administration of 1,200 mg miconazole suppository on Day 8 of ANNOVERA use increased the systemic exposure of EE (AUCDay8-21) by approximately 67%. A similar trend was observed with SA with AUCDay8-9, AUCDay8-10, and AUCDay8-21 increasing by approximately 30%, 32%, and 19%, respectively. When 200 mg miconazole vaginal suppositories were administered on Day 8, Day 9, and Day 10 of ANNOVERA use, EE AUCDay8-11 and AUCDay8-21 were increased by 9% and 42%, respectively. SA AUCDay8-11 and AUCDay8- 21 were increased by 28% and 27%, respectively. Water-based vaginal miconazole cream had no effect on ANNOVERA [see Drug Interactions (7.3)].

The in vitro studies suggest that SA is unlikely to inhibit or induce CYP enzymes at the therapeutic dose.

13 NONCLINICAL TOXICOLOGY

13.1 Carcinogenesis, Mutagenesis, Impairment of Fertility

Carcinogenesis

In a 2-year carcinogenicity study in rats with subdermal implants releasing 40, 100, and 200 mcg segesterone acetate per day (approximately 17–86 times the daily dose of segesterone acetate in females using ANNOVERA, based on body surface area), no drug-related increase in tumor incidence was observed. In a 2-year intravaginal carcinogenicity study in mice, segesterone acetate gel produced an increased incidence of adenocarcinoma and lobular hyperplasia in the breast at a dose of 30 mg/kg/day, approximately 10 times the systemic exposure of segesterone acetate per day in females using ANNOVERA, based on AUC. A dose of 10 mg/kg/day in the mouse, approximately 3 times the systemic exposure of segesterone acetate per day based on AUC, did not result in carcinogenic findings.

Long-term continuous administration of natural and synthetic estrogens in certain animal species increases the frequency of carcinomas of the breast, uterus, cervix, vagina, testis, and liver.

Mutagenesis

Segesterone acetate was neither mutagenic nor clastogenic in the Ames/Salmonella reverse mutation assay, the chromosomal aberration assay in Chinese hamster ovary cells, or in the in vivo mouse micronucleus test.

Impairment of Fertility

A return to fertility study was conducted with segesterone acetate in rats, using subdermal implants releasing a dose approximately 25 times the anticipated daily vaginal human dose (based on body surface area). Three months of treatment with segesterone acetate suppressed fertility, but 7 weeks after cessation of treatment, there were no adverse effects on ovulation or resulting litter parameters.

14 CLINICAL STUDIES

The efficacy of ANNOVERA was evaluated in two 1-year multicenter trials enrolling 2,265 females, age 18–40 years, who were healthy and sexually active with regular menstrual cycles. The trials were conducted in the U.S., Dominican Republic, Brazil, Chile, Finland, Hungary, Sweden, and Australia, with 67.1% of females from the U.S. The racial/ethnic distribution was Caucasian (71.2%), African-American (14.1%), Asian (3.5%), other/multiple races (11.2%); 28.7% of the study population was Hispanic. The mean age was 26.7 years and the mean (range) BMI was 24.1 (16.0, 41.5) kg/m^2. At approximately 50% enrollment, women with BMI >29.0 kg/m^2 were no longer enrolled in the two trials and all women with a BMI >29.0 kg/m^2 were discontinued from the trials.

Based on pooled data from the two trials, 2,111 females ≤35 years of age completed 17,427 evaluable 28-day cycles (cycles in which no back-up contraception was used). The pooled pregnancy rate, evaluated by the Pearl Index (PI), was 2.98 (95% Confidence Interval [2.13, 4.06]) per 100 woman-years of ANNOVERA use.

Return to fertility was assessed in 290 of the subjects in the two trials who either desired pregnancy or switched to a nonhormonal method after the trials, and all 290 subjects reported a return to fertility during the 6-month follow-up period (defined as a return of menses or pregnancy).

15 REFERENCES

1. Dinger, J, Mohner S, Heinemann K. Cardiovascular risk associated with the use of an etonogestrel- containing vaginal ring. Obstetrics & Gynecology 2013; 122(4): 800-808.
2. Sidney, S, Cheetham TC, Connell FA, Oullet-Hellstrom R, Graham DJ, Davis D,, Recent combined hormonal contraceptives (CHCs) and the risk of thromboembolism and other cardiovascular events in new users. Contraception 2013; 87: 93–100.
3. Combined hormonal contraceptives (CHCs) and the risk of cardiovascular endpoints. Sidney, S. (primary author) http://www.fda.gov/downloads/Drugs/DrugSafety/UCM277384.pdf, accessed 04- April-2019.

16 HOW SUPPLIED/STORAGE AND HANDLING

16.1 How Supplied

ANNOVERA (segesterone acetate and ethinyl estradiol vaginal system) is a toroidal- shaped (ring), nonbiodegradable, flexible, opaque white vaginal system. The vaginal system body has an overall diameter of 56 mm and a cross-sectional diameter of 8.4 mm. When placed inside the vagina, each ANNOVERA releases an approximate average 0.15 mg/day of segesterone acetate and 0.013 mg/day of ethinyl estradiol over 21-day in-use period of each cycle for up to 13 cycles (total 273 days). Each cycle is 28 days, with 21 days in and 7 days out.

Each ANNOVERA is individually packaged in an aluminum pouch. The pouch consists of a laminate from outside to inside of polyester, aluminum foil, and polyethylene.

First insertion of ANNOVERA must be prior to the date of expiration. Discard one year after first insertions.

A black compact case is provided with the drug product for storage of ANNOVERA by patients during each 7-day vaginal system-out interval.

The vaginal system should be placed in the compact case after 13 cycles of use and discarded via a drug take-back option if one is available. If a take-back option is unavailable, then discard in the waste receptacle out of reach of children and pets. The vaginal system should NOT be flushed down the toilet. See www.fda.gov/drugdisposal for more information about disposal of medicines.

Each box contains 1 ANNOVERA vaginal system in a pouch and 1 storage case.

NDC 68308-752-01

16.2 Storage Conditions

Prior to dispensing ANNOVERA to the user, store ANNOVERA at 20°C to 25°C (68°F to 77°F), excursions permitted to 15°C to 30°C (59°F to 86°F) [see USP Controlled Room Temperature].

Protect ANNOVERA from direct sunlight.

Do not refrigerate or freeze and avoid excessive heat.

17 PATIENT COUNSELING INFORMATION

Advise the patient to read the FDA-approved patient labeling (Patient Information and Instructions for Use).

Cigarette Smoking

Cigarette smoking increases the risk of serious cardiovascular events from CHC use, and females who are over 35 years old and smoke should not use ANNOVERA [see Boxed Warning and Warnings and Precautions (5.1)].

Venous Thromboembolism

Increased risk of VTE compared to nonusers of CHCs is greatest after initially starting a CHC or restarting (following a 4-week or greater dose-free interval) the same or a different CHC [see Warnings and Precautions (5.1)].

Sexually Transmitted Infections

ANNOVERA does not protect against HIV-infection (AIDS) and other sexually transmitted infections. ANNOVERA is compatible with male condoms made with natural rubber latex, polyisoprene, and polyurethane.

Use During Pregnancy

ANNOVERA is not to be used during pregnancy; instruct the patient to remove ANNOVERA if pregnancy is confirmed during treatment [see Use in Specific Populations (8.1)].

ANNOVERA Dosing and Instructions

Advise the woman on proper use of ANNOVERA and what to do if she does not comply with the labeled timing of insertion and removal. The efficacy of ANNOVERA is greatest when ANNOVERA is kept in the vagina continuously for the scheduled 21 consecutive days. Removal of ANNOVERA even briefly during the scheduled 21 days of use can reduce efficacy.

ANNOVERA should be washed with mild soap and water and rinsed and patted dry with a clean cloth towel or paper towel prior to each insertion and at each removal. Prior to initial use, the storage case should be labeled with the discard date to avoid using the product beyond 13 cycles [see Dosage and Administration (2) and FDA-approved Patient Information].

Place the completely used ANNOVERA in the case provided and discard via a drug take- back option if one is available. If a take-back option is unavailable, then discard in the waste receptacle out of reach of children and pets. The vaginal system should NOT be flushed down the toilet. See www.fda.gov/drugdisposal for more information about disposal of medicines. [see How Supplied (16.1)].

Use with Vaginal Products

Water-based vaginal lubricants have no effect on the vaginal system; however, oil-based (including silicone-based) vaginal lubricants will alter the vaginal system and/or exposure to EE and SA and should not be used [see Drug Interactions (7.3)].

Need for Additional Contraception

Use a back-up or alternative method of contraception when:

Enzyme inducers are used with CHCs [see Drug Interactions (7.1)].
  ANNOVERA has been out for more than 2 hours cumulative during the 21 days of continuous use or the vaginal system-free interval exceeds 7 days [see Dosage and Administration (2.3)].

Postpartum females who have not yet had a period should use an additional method of contraception until ANNOVERA has been in place for 7 consecutive days [see Dosage and Administration (2.2)].

Lactation

ANNOVERA may reduce breast milk production. This is less likely to occur if breastfeeding is well established. Females who are breastfeeding should not use ANNOVERA until after weaning [see Use in Specific Populations (8.2)].

Amenorrhea and Possible Symptoms of Pregnancy

Amenorrhea may occur. Consider pregnancy in the event of amenorrhea and rule out pregnancy if amenorrhea is associated with symptoms of pregnancy, such as morning sickness or unusual breast tenderness [see Warnings and Precautions (5.9)].

Fertility Following Discontinuation of ANNOVERA

Resumption of fertility after discontinuation of ANNOVERA is expected. All women followed for return of fertility experienced a return of fertility by 6 months after discontinuing ANNOVERA [see Clinical Studies (14)].

Patient Information
ANNOVERA® (ann-o-VER-ah)
(segesterone acetate and ethinyl estradiol vaginal system)

Read this Patient Information carefully before you decide if ANNOVERA is right for you. This information does not take the place of talking with your gynecologist or other healthcare provider who specializes in women's health. If you have any questions about ANNOVERA, ask your healthcare provider. You should also learn about other birth control methods to choose the one that is best for you.

What is the most important information I should know about ANNOVERA?

- Do not use ANNOVERA if you smoke cigarettes and are over 35 years old.
  Smoking increases your risk of serious heart and blood vessel (cardiovascular) side effects from hormonal birth control methods, including death from heart attack, blood clots, or stroke. This risk increases with age and the number of cigarettes you smoke.

ANNOVERA does not protect against HIV infection (AIDS) and other sexually transmitted infections (STIs).

What is ANNOVERA?
ANNOVERA is a hormone-releasing system used by females who are able to become pregnant to prevent pregnancy. You insert ANNOVERA into your vagina. ANNOVERA is in the shape of a ring that is reusable for 1 year. The vaginal system is made of silicone and contains two female hormones that are slowly released into your vagina and then enter your blood. One hormone is an estrogen called ethinyl estradiol. The other hormone is a progestin called segesterone acetate.

How well does ANNOVERA work for contraception?
Your chance of getting pregnant depends on how well you follow the directions for using the vaginal system. The more carefully you follow the directions, the less chance you have of getting pregnant.
Based on the results of two clinical studies that lasted 12 months, about 2 to 4 women out of 100 women may get pregnant during the first year they use ANNOVERA. ANNOVERA was designed to be reused for 1 year. Replace ANNOVERA at the end of 1 year if you choose to continue using ANNOVERA. There is not enough hormone left in the vaginal system to provide you effective birth control after 1 year of use.
The following chart shows the chance of getting pregnant for women who use different methods of birth control. Each box on the chart contains a list of birth control methods that are similar in how well they work to prevent pregnancy. The most effective methods are at the top of the chart. The box at the bottom of the chart shows the chance of getting pregnant for women who do not use birth control and are trying to get pregnant.
ANNOVERA, a vaginal system with hormones, is in the second box from the top of the chart.

Who should not use ANNOVERA?
Do not use ANNOVERA if you:

- smoke and are over 35 years old.
- have or have had a blood clot in your arms, legs, lungs, or eyes.
- have had a stroke.
- have reduced blood flow to your brain (cerebrovascular disease).
- have reduced blood flow or blockage in 1 or more of the arteries that supply blood to your heart (coronary artery disease).
- have had a heart attack.
- have heart rhythm or heart valve problems that increase your risk of having blood clots, such as an infection of the inner lining of the heart and heart valves or a type of irregular heartbeat called atrial fibrillation.
- have a problem with your blood that makes it clot more than normal.
- have high blood pressure that is not controlled with medicine or have high blood pressure with blood vessel damage.
- have diabetes and are over 35 years old; have diabetes with high blood pressure or problems with your kidneys, blood vessels, eyes, or nerves; or have had diabetes for longer than 20 years.
- have headaches with changes in vision, numbness or weakness, have migraine headaches with aura, or are over age 35 years old and have any type of migraine headaches.
- have liver disease or liver tumors.
- have or have had breast cancer or any cancer that is sensitive to the female hormones estrogen or progesterone.
- have unexplained vaginal bleeding.
- are allergic to segesterone acetate, ethinyl estradiol, or any of the ingredients in ANNOVERA. See the end of this leaflet for a complete list of ingredients in ANNOVERA.
- take any Hepatitis C drug combination medicine containing ombitasvir/paritaprevir/ritonavir, with or without dasabuvir. This may increase levels of the liver enzyme alanine aminotransferase (ALT) in the blood.

What should I tell my healthcare provider before using ANNOVERA?
Before you use ANNOVERA tell your healthcare provider if you:

- have any of the conditions listed above.
- smoke.
- are pregnant or think you are pregnant.
- recently had a baby, miscarriage, or abortion.
- have breast problems such as an abnormal mammogram or breast x-ray, breast nodules, fibrocystic breast disease, or a family history of breast cancer.
- have any medical condition, especially migraine headaches, depression, seizures, diabetes, high blood pressure, high cholesterol or triglycerides, gallbladder disease, liver disease, heart disease, or kidney disease.
- have a family history of blood clots or stroke.
- have yellowing of the skin or eyes (jaundice).
- have a condition that makes your vagina become irritated easily.
- have a history of toxic shock syndrome.
- had gallbladder problems when you were pregnant.
- are scheduled for surgery. The hormones in ANNOVERA may increase your risk of blood clots after surgery. You should stop using ANNOVERA at least 4 weeks before you have surgery and not restart until at least 2 weeks after your surgery.
- are scheduled for any laboratory tests. Certain blood tests may be affected by hormonal birth control methods.
- are breastfeeding or plan to breastfeed. You should not use ANNOVERA if you are breastfeeding. The hormones in ANNOVERA may decrease your milk production. The hormones in ANNOVERA pass into your breast milk. Talk with your healthcare provider about the best birth control method for you while breastfeeding.

Tell your healthcare provider about all medicines you take, including prescription and over-the-counter medicines, vitamins, and herbal supplements. Some medicines, vitamins, and herbal supplements make hormonal contraception less effective, such as:

- anti-seizure medicines
- medicine used to treat fungal infections
- combinations of HIV medicines
- Hepatitis C (HCV) medicines
- non-nucleoside reverse transcriptase inhibitors medicine to
- treat tuberculosis
- medicine to treat high blood pressure in the vessels of the lung medicine to
- treat chemotherapy-induced nausea and vomiting
- St. John's wort

Talk to your healthcare provider if you take any of the medicines listed above to see if the specific medicine you take may make hormonal contraceptives less effective. Use a back-up or another birth control method when you take medicine that may make hormonal contraceptives less effective and for 28 days after stopping the medicine.
Do not use any vaginal products such as oil-based suppositories, oil-based creams, or oil-based gels while the vaginal system is in your vagina. Do not use any vaginal lubricants that have silicone or oil in them. Water-based lubricants are ok to use. Be sure to read the ingredients on the label carefully before you buy a vaginal lubricant.
Some medicines and grapefruit juice may increase the level of ethinyl estradiol in your blood if used together, including:

- the pain reliever acetaminophen
- ascorbic acid (vitamin C)
- types of medicines used to treat fungal infections
- HIV medicines
- non-nucleoside reverse transcriptase inhibitors medicines to
- lower cholesterol

ANNOVERA may affect the way that lamotrigine (a medicine used to treat seizures) works and may increase the risk of seizures. Your healthcare provider may need to adjust your dose of lamotrigine.
Females who take thyroid hormone replacement medicine or corticosteroid replacement medicine may need increased doses of their thyroid hormone or cortisol medicines.
Ask your healthcare provider if you are not sure if you take any of the medicines listed above.
Know the medicines you take. Keep a list of them to show your healthcare provider and pharmacist when you get a new medicine. Talk to your healthcare provider before you start taking a new medicine.

How should I use ANNOVERA?

- Read the Instructions for Use at the end of this Patient Information that comes with ANNOVERA for information about the right way to insert, remove, clean, store, and dispose of (throw away) ANNOVERA.
- Use ANNOVERA exactly as your healthcare provider tells you to use it.

ANNOVERA is a hormonal birth control method that is used for 3 out of 4 weeks every month. The same vaginal system is reusable for up to 1 full year (1 year includes 13 cycles; each cycle is 28 days).
After you insert ANNOVERA for the first time, you will remove it at the end of week 3 and leave it out for 7 days. You will reinsert ANNOVERA at the end of week 4 of each 4- week cycle. You will repeat this pattern with ANNOVERA for up to 13 cycles. Scheduled insertions and removals of ANNOVERA should be at about the same time of the day and the same day of the week for each monthly cycle.

- The day of the week when you first insert ANNOVERA (referred to as "Day 1") is your vaginal system change day.
- For each cycle, you put the vaginal system into your vagina and let it stay there 3 weeks (21 full days). Remember to keep the vaginal system in for the whole 3 weeks (21 full days).
- You take the vaginal system out on your vaginal system change day (Day 22) and let it stay out for 1 week (7 full days). Note that your vaginal system should be cleaned with warm water and mild soap, dried with a clean cloth towel or paper towel, and stored in the case provided, away from children, pets, and extreme temperatures. (See the Instructions for Use.)
- Then you start over again for another 4 weeks. You may not be bleeding when you put the vaginal system in.
- Always put the vaginal system in or take it out on your vaginal system change day at about the same time of day. For example, if you put your vaginal system in on Monday at 9:00 in the morning, always take it out or put it back in on Monday at about 9:00 in the morning.
- You do not have to take the vaginal system out when you have sex. If you decide to remove it, remember to reinsert it within 2 hours after removing it or you may not be protected from pregnancy. However, if ANNOVERA is out of your vagina for more than 2 hours at one time or if ANNOVERA is out of your vagina at different times that add up to more than a total of 2 hours over the first 21 days of your cycle, you will need to use another method of birth control (such as male condoms or spermicide) until ANNOVERA has been in your vagina for 7 days in a row.

The diagram shows the timing for putting the vaginal system in and taking it out for 2 cycles.

Schedule

Cycle 1

Put vaginal system in →
(vaginal system change day)

Day 1

Weeks 1, 2, and 3
Days 1-21

Take vaginal system out→
(vaginal system change day)

Day 22

Week 4
Days 22-28

Cycle 2
(repeat for Cycles 3-13)

Put vaginal system in→
(vaginal system change day)

Day 1

Weeks 1, 2, and 3
Days 1-21

Take vaginal system out→
(vaginal system change day)

Day 22

Week 4
Days 22-28

- Repeat the 4-week cycle for all 13 cycles of the use of the vaginal system.
- Do not use the vaginal system for more than 13 cycles (1 year). At the end of the 13 cycles, take the vaginal system out of your vagina. Place the used vaginal system in the case that comes with ANNOVERA and dispose of it (throw away) at a drug take-back location, if available. If a drug take-back location is not available, dispose of it in the trash out of reach of children and pets. Do not flush ANNOVERA down the toilet.
  - If you want to continue using ANNOVERA after 13 cycles, you will need to receive a new prescription from your healthcare provider for a new vaginal system.
- If you start using ANNOVERA 4 or more weeks after having a baby and you have not had a menstrual period yet, you should use another method of birth control until you have used ANNOVERA for 7 days in a row.

What happens if I am off schedule using the vaginal system?
It is very important to follow the schedule every cycle and remove and insert ANNOVERA on your vaginal system-in and vaginal system-out days at about the same time. If you take the vaginal system out too soon or put it back in too late, your chance of getting pregnant is higher.
If you are more than 1 or 2 days off schedule for vaginal system insertion you will need to use new vaginal system-in and vaginal system-out days for the remaining cycles of use. You will also need to use back-up contraception, such as condoms or spermicide, for the first 7 days of the new schedule if you have sexual intercourse.

If you put the vaginal system back in:

Then:

Too early, after it had been out for only 5 or 6 days.

Keep the vaginal system in for at least 3 weeks (21 days). You may keep it in up to your normal vaginal system-out day.

Too late, after it had been out for more than 7 days.

Put the vaginal system back in right away. You will now have a new vaginal system-in day. You must use condoms or spermicide as back-up contraception for the next 7 days when you have sexual intercourse.

If you took the vaginal system out:

Then:

Too early, after it had been in for only 19 or 20 days.

Leave the vaginal system out for 1 week. Put it back in after the week is over, as you would normally do. You may then keep it in up to your normal vaginal system-out day, 22 or 23 days after you put the vaginal system in.

Too late, after it had been in for 22 or 23 days.

Remove the vaginal system as soon as you realize this. Then reinsert the vaginal system 7 days later.

During the 21 days of continuous use, if ANNOVERA is out of the vagina for more than 2 continuous hours or more than 2 cumulative hours (multiple inadvertent removals or expulsions adding up to 2 hours), then back-up contraception such as male condoms or spermicide should be used until the vaginal system has been in the vagina for 7 consecutive days.

What if I miss my menstrual period or if I think I am pregnant?
It is possible that you are pregnant if you miss your scheduled period (no bleeding on the 7 days that the vaginal system is out). Tell your healthcare provider right away that you have missed your period. Also, tell your healthcare provider if you have symptoms of pregnancy such as morning sickness or unusual breast tenderness. It is important that your healthcare provider check you to find out if you are pregnant. You may need a pregnancy test to determine if you are pregnant. Do not remove the vaginal system until you are certain you are pregnant. Stop using ANNOVERA if your healthcare provider tells you that you are pregnant.

What are the possible side effects of ANNOVERA? ANNOVERA can cause serious side effects, including:
See: "What is the most important information I should know about ANNOVERA?"

- blood clots. Like pregnancy, hormonal contraceptives increase the risk of serious blood clots, especially in women who have other risk factors, such as smoking, obesity, or age greater than 35. This increased risk is highest when you first start taking hormonal contraceptives and when you restart the same or different hormonal contraceptive after not using it for 4 weeks or more.
  It is possible to die or be permanently disabled from a problem caused by a blood clot, such as a heart attack or a stroke. Some examples of serious blood clots are blood clots in the:
    - legs (deep vein thrombosis)
    - lungs (pulmonary embolus)
    - eyes (loss of eyesight)
    - heart (heart attack)
    - brain (stroke)
  Call your healthcare provider or get emergency medical care right away if you have:
    - leg pain that does not go away
    - sudden shortness of breath
    - sudden changes in vision or blindness
    - severe pain or pressure in your chest
    - a sudden, severe headache unlike your usual headaches
    - weakness or numbness in an arm or leg
    - trouble speaking
- toxic shock syndrome (TSS). Some symptoms of TSS are the same as flu symptoms, but they can become serious very quickly. Call your healthcare provider or get emergency medical care right away if you have he following symptoms:

- sudden high fever
- vomiting
- diarrhea
- fainting or feeling faint when standing up

- a sunburn-like rash
- muscle aches
- dizziness

- liver problems, including liver tumors. Tell your healthcare provider right away if you have yellowing of your skin or eyes (jaundice).
- high blood pressure
- gallbladder problems or worsening of a gallbladder problem you already have. You may have an increased risk of gallbladder problems with the use of ANNOVERA if you had gallbladder problems when you were pregnant.
- changes in the sugar and fat (cholesterol and triglycerides) levels in your blood.
- headache. Tell your healthcare provider if you have new headaches that keep coming back, that do not go away, or are severe. Also tell your healthcare provider if your migraine headaches happen more often or are more severe than normal.
- irregular or unusual vaginal bleeding and spotting between your menstrual periods, especially during the first month of using ANNOVERA, or the absence of menstrual periods (amenorrhea).
- depression.
- possible cancer in your cervix.
- swelling of your skin especially around your mouth, eyes, and in your throat (angioedema). Call your healthcare provider or get emergency medical care right away if you have a swollen face, lips, mouth, tongue, or throat as this may lead to difficulty swallowing or breathing. Your risk of having angioedema is higher if you have a history of angioedema.
- dark patches of skin on your forehead, cheeks, upper lip, and chin (chloasma). Your risk of getting chloasma with the use of ANNOVERA is higher if you had chloasma during pregnancy. Women who tend to get chloasma should avoid spending a long time in sunlight, tanning booths, and under sunlamps while using ANNOVERA. Use sunscreen if you have to be in the sunlight.

The most common side effects of ANNOVERA include:

- headache, including migraine
- nausea/vomiting
- vaginal yeast infection (candidiasis)
- lower/upper abdomen pain
- painful periods
- vaginal discharge

- urinary tract infection
- breast pain/tenderness
- irregular vaginal bleeding
- diarrhea
- genital itching

This is not a complete list of possible side effects. Call your healthcare provider for medical advice about side effects. You may report side effects to FDA at 1-800-FDA-1088. You may also report side effects to Mayne Pharma at 1-844-825-8500.
No serious problems have been reported from a hormonal contraceptive overdose.

Does hormonal birth control cause cancer?
It is not known if hormonal birth control causes breast cancer. Some studies, but not all, suggest that there could be a slight increase in the risk of breast cancer among current users with longer duration of use.
If you have breast cancer now, or have had it in the past, do not use hormonal birth control because some breast cancers are sensitive to hormones.
Women who use hormonal contraceptives may have a slightly higher chance of getting cervical cancer. However, this may be due to other reasons such as having more sexual partners.

What should I know about my period when taking ANNOVERA?
When you take ANNOVERA you should expect to have regular 28-day cycles. Each period is likely to last about 5 days. You may have bleeding or spotting between your scheduled periods especially during the first cycle. This bleeding or spotting tends to decrease after the first cycle. Do not stop taking ANNOVERA because of this bleeding or spotting. If the spotting continues for more than 7 consecutive days or if the bleeding is unusually heavy, call your healthcare provider.
Tell your healthcare provider if you do not have your period.

What if I want to become pregnant?
You may stop using ANNOVERA whenever you wish. Consider a visit with your healthcare provider for a pre-pregnancy checkup before you stop taking ANNOVERA.

General information about the safe and effective use of ANNOVERA.
Medicines are sometimes prescribed for purposes other than those listed in a Patient Information leaflet. Do not use ANNOVERA for a condition for which it was not prescribed. Do not give ANNOVERA to other people, even if they have the same symptoms that you have. It may harm them. You can ask your healthcare provider or pharmacist for information about ANNOVERA that is written for health professionals.

What if I have other questions?
If you have concerns or questions, ask your healthcare provider.

What are the ingredients in ANNOVERA?
Active ingredients: segesterone acetate and ethinyl estradiol.
Inactive ingredients: dibutyltin dilaurate, silicone elastomers, silicone medical adhesive, and titanium dioxide.

Instructions for Use

ANNOVERA® (ann-o-VER-ah)

(segesterone acetate and ethinyl estradiol vaginal system)

Read this Instructions for Use carefully before you decide if ANNOVERA is right for you. This information does not take the place of talking with your gynecologist or other healthcare provider who specializes in women's health. If you have any questions about ANNOVERA, ask your healthcare provider. You should also learn about other birth control methods to choose the one that is best for you.

How should I start using ANNOVERA?

If you are not currently using hormonal birth control, start using ANNOVERA between Days 2 and 5 of your menstrual period.

- If your menstrual periods are not regular or if you start using ANNOVERA more than 5 days from when you started your menstrual period, you should use a barrier method of birth control, such as a male condom or spermicide during sexual intercourse for the first 7 days you use ANNOVERA.

If you are changing from a birth control pill or patch or monthly disposable contraceptive vaginal ring to ANNOVERA:

- If you have been using your birth control method correctly and are certain that you are not pregnant, you can change to ANNOVERA any day of your birth control cycle. Do not start ANNOVERA any later than the day you would start your next birth control pill, apply your next patch or insert your next monthly disposable contraceptive vaginal ring.

If you are changing from a progestin-only birth control method, such as a minipill, injection, implant or intrauterine system (IUS):

- You may switch from a minipill on any day. Start using ANNOVERA on the day that you would have taken your next minipill.
- You should switch from an injectable and start using ANNOVERA on the day when your next injection would be due.
- You should switch from an implant or the IUS and start using ANNOVERA at the time the implant or IUS is removed.

If you are changing from a minipill, injection, implant, or an intrauterine system to ANNOVERA, you should use a barrier method of birth control, such as a male condom or spermicide, during sexual intercourse for the first 7 days you use ANNOVERA.

If you start using ANNOVERA after an abortion or miscarriage:

- Following a first trimester abortion or miscarriage: You may start ANNOVERA within 5 days following a first trimester abortion or miscarriage (the first 12 weeks of pregnancy). You do not need to use an additional birth control method.
  - If you do not start ANNOVERA within 5 days after a first trimester abortion or miscarriage, use a non-hormonal birth control method, such as male condoms or spermicide, while you wait for your menstrual period to start. Start using ANNOVERA between days 2 and 5 of your menstrual period.
  - If you start using ANNOVERA more than 5 days from when you started your menstrual period, you should use a barrier method of birth control, such as a male condom or spermicide during sexual intercourse for the first 7 days you use ANNOVERA.
- Following a second trimester abortion or miscarriage: You may start using ANNOVERA no sooner than 4 weeks (28 days) after a second trimester abortion (after the first 12 weeks of pregnancy).

If you are starting ANNOVERA after childbirth:

- You may start using ANNOVERA no sooner than 4 weeks (28 days) after having a baby if you are not breastfeeding.
- If you have not gotten your menstrual period after childbirth, you should talk to your healthcare provider. You may need a pregnancy test to make sure you are not pregnant before you start using ANNOVERA.
- Use another birth control method, such as a male condom or spermicide, during sexual intercourse for the first 7 days you use ANNOVERA if you have not yet had a period.

If you are breastfeeding, you should not use ANNOVERA. Use other birth control methods until you are no longer breastfeeding.

How do I use ANNOVERA?

Step 1. Open the package and remove ANNOVERA.

- Wash your hands with mild soap and water. Dry them well.
- Take ANNOVERA out of its package (See Figure, Step 1).
- Wash ANNOVERA with mild soap and water, rinse and pat dry with a clean cloth towel or paper towel.

Step 2. Prepare to insert ANNOVERA.

- Hold ANNOVERA between your thumb and first (index) finger.
- Press the sides of ANNOVERA together to make it narrow (See Figure, Step 2).

Step 3. Choose a position for insertion of ANNOVERA.

- Choose the position that is comfortable for you. For example, lying down, squatting, or standing with 1 leg up (See Figures, Steps 3-A, 3-B, 3-C).

Step 4. Insert ANNOVERA into your vagina.

- Gently insert the folded ANNOVERA into your vagina (See Figure, Step 4-A).
- Push ANNOVERA further up into your vagina using your index finger.
- Push it in as far as you can. It sometimes helps to push down with the muscles in your vagina while you are inserting ANNOVERA.
- When you insert ANNOVERA, it may be in different positions in your vagina, but ANNOVERA does not have to be in an exact position for it to work.
- Mark your vaginal system "in day" on your calendar.

Note:

- If you feel the ANNOVERA in your vagina or if it feels uncomfortable, you may not have pushed the ANNOVERA into your vagina far enough. Use your index finger to gently push ANNOVERA as far as you can into your vagina (See Figure, Step 4- B). There is no danger of ANNOVERA being pushed too far up in the vagina or getting lost.
  - You should not feel ANNOVERA after you have placed it into your vagina.
- Some women and their partners may be aware of ANNOVERA in the vagina during sexual intercourse.

Step 5. How do I remove ANNOVERA?

- Wash and dry your hands.
- Choose the position that is most comfortable for you (See Step 3).
- Put your index finger into your vagina and hook it through ANNOVERA. Gently pull downward and forward to remove ANNOVERA and pull it out (See Figure, Step 5). It sometimes helps to push down with the muscles in your vagina while you are removing ANNOVERA.
- Wash the ANNOVERA vaginal system with mild soap and lukewarm water, pat it dry, and store in the case provided.
- Mark your vaginal system "out day" on your calendar.

What else should I know about ANNOVERA?

- The day of the week when you first insert ANNOVERA (called "Day 1") is your vaginal system change day. This is described further in the Patient Information section entitled "How should I use ANNOVERA?"
- For each cycle, you put the vaginal system into your vagina and let it stay there 3 weeks (21 full days). Remember to keep the vaginal system in for the whole 3 weeks (21 full days).
- You take the vaginal system out on your vaginal system change day (Day 22) and let it stay out for 1 week (7 full days). Note that your vaginal system should be stored in the case provided, away from children, pets, and extreme temperatures.
- Then you start over again for another 4 weeks. You may not be bleeding when you put the vaginal system in.
- Always put the vaginal system in or take it out on your vaginal system change day at about the same time of day. For example, if you put your vaginal system in on Monday at 9:00 in the morning, always take it out or put it back in on Monday at about 9:00 in the morning.
- You do not have to take the vaginal system out when you have sex. If you decide to remove it, remember to reinsert it within 2 hours after removing it or you may not be protected from pregnancy. However, if ANNOVERA is out of your vagina for more than 2 hours at one time or if ANNOVERA is out of your vagina at different times that add up to more than a total of 2 hours over the first 21 days of your cycle, you will need to use another method of birth control until ANNOVERA has been in your vagina for 7 days in a row, such as male condoms or spermicides.
- Repeat the 4-week cycle for all 13 cycles of the use of the vaginal system.
- Do not use the vaginal system for more than 13 cycles (1 year). When you take the vaginal system out of your vagina at the end of the 13 cycles, dispose of it. See "How should I dispose of (throw away) ANNOVERA?" below.
- If you want to continue using ANNOVERA after 13 cycles, you will need to get a new prescription from your healthcare provider to obtain a new vaginal system.
- Do not to use any vaginal products such as oil-based suppositories, oil-based creams, or oil-based gels while the vaginal system is in your vagina. Do not use any vaginal lubricants that have silicone or oil in them. Water-based lubricants are ok to use. Be sure to read the ingredients on the labels carefully before you buy a vaginal lubricant.
- First insertion of ANNOVERA must be prior to the date of expiration. Discard one year after first insertion. See "How should I dispose of (throw away) ANNOVERA?" below.
- Do not take any medicines unless your healthcare provider says it is ok to take them.
  Tell your healthcare provider when you start a new medicine.

How do I clean ANNOVERA?

- After removing ANNOVERA from your vagina, wash it with mild soap and warm water, rinse, and pat it dry with a clean cloth towel or paper towel before you store it. Only use mild soap and warm water to clean.
- Wash ANNOVERA with mild soap and warm water and pat it dry before you put it back into your vagina.
- Store ANNOVERA in the case provided.

How should I store ANNOVERA?

- Store ANNOVERA in the supplied case at room temperature between 68°F to 77°F (20°C to 25°C).
- Protect ANNOVERA from direct sunlight.
- Do not refrigerate or freeze ANNOVERA.
- Avoid storing ANNOVERA in extreme heat.
- Keep ANNOVERA and all medicines out of the reach of children and pets.

How should I dispose of (throw away) ANNOVERA?

- After 13 cycles of use, place ANNOVERA in the case that comes with it.
- Dispose of ANNOVERA at a drug take-back location, if available. If a drug take-back location is not available, dispose of ANNOVERA in the trash, out of the reach of children and pets.
- Do not throw away ANNOVERA in the toilet.
- See www.fda.gov/drugdisposal for more information about disposal of medicines.

When does ANNOVERA become effective?

ANNOVERA becomes effective on the day it is inserted (Day 1), if it is inserted between Days 2 and 5 of your menstrual period. If ANNOVERA is inserted more than 5 days from when you start your menstrual period, you should use a barrier method of birth control, such as a male condom or spermicide, during sexual intercourse for the first 7 days you use ANNOVERA.

Will ANNOVERA interfere during sexual intercourse?

- If ANNOVERA is placed as high as possible in your vagina, it will not interfere with sexual intercourse.

Can I take ANNOVERA out during the first 3 weeks of my cycle?

- You should leave ANNOVERA in the entire 21 days (3 weeks).
  - If ANNOVERA comes out or if you remove it, put it back in as soon as possible. If you put ANNOVERA back into your vagina before 2 hours has passed, you do not need to use another method of birth control. However, if ANNOVERA is out of your vagina for more than 2 hours at one time or if ANNOVERA is out of your vagina at different times that add up to more than a total of 2 hours over the first 21 days of your cycle, you will need to use another method of birth control until ANNOVERA has been in your vagina for 7 days in a row, such as male condoms or spermicides.

What should I do if ANNOVERA comes out of my vagina?

ANNOVERA can slip or accidentally come out of your vagina (expelled), for example, during sexual intercourse, bowel movements, or use of tampons.

- If ANNOVERA slips out of your vagina, wash ANNOVERA with mild soap and warm water, rinse and pat dry with a clean cloth towel or paper towel and put it back in your vagina right away or within 2 hours. See "Can I take ANNOVERA out during the first 3 weeks of my cycle?" in the section above.
- ANNOVERA can move around and become visible at the opening of your vagina. If this happens follow "Step 4" above for directions on how to push ANNOVERA back to its right position.

What if I lose ANNOVERA?

- Call your healthcare provider right away if you lose ANNOVERA. You should use a back-up method of birth control such as a male condom or spermicide for preventing pregnancy until you get a new ANNOVERA.

If you have other questions call your healthcare provider.

For information, call Mayne Pharma at 1-844- 825-8500

Distributed by:
Mayne Pharma
Raleigh, NC 27609

ANNOVERA is a registered trademark of Population Council and licensed under license.

The Patient Information and Instructions for Use have been approved by the U.S. Food and Drug Administration.

Revised 08/2024

PRINCIPAL DISPLAY PANEL - 30 Ring Pouch Carton

NDC 68308-752-01
Rx only

Annovera®
(segesterone acetate and
ethinyl estradiol vaginal system)
Delivers 0.15 mg/0.013 mg per day

This product is intended to prevent pregnancy.
It does not protect against HIV infection (AIDS)
and other sexually transmitted diseases.

Keep out of reach of children and pets

For Vaginal Use
CONTAINS 1 VAGINAL SYSTEM

mayne pharma